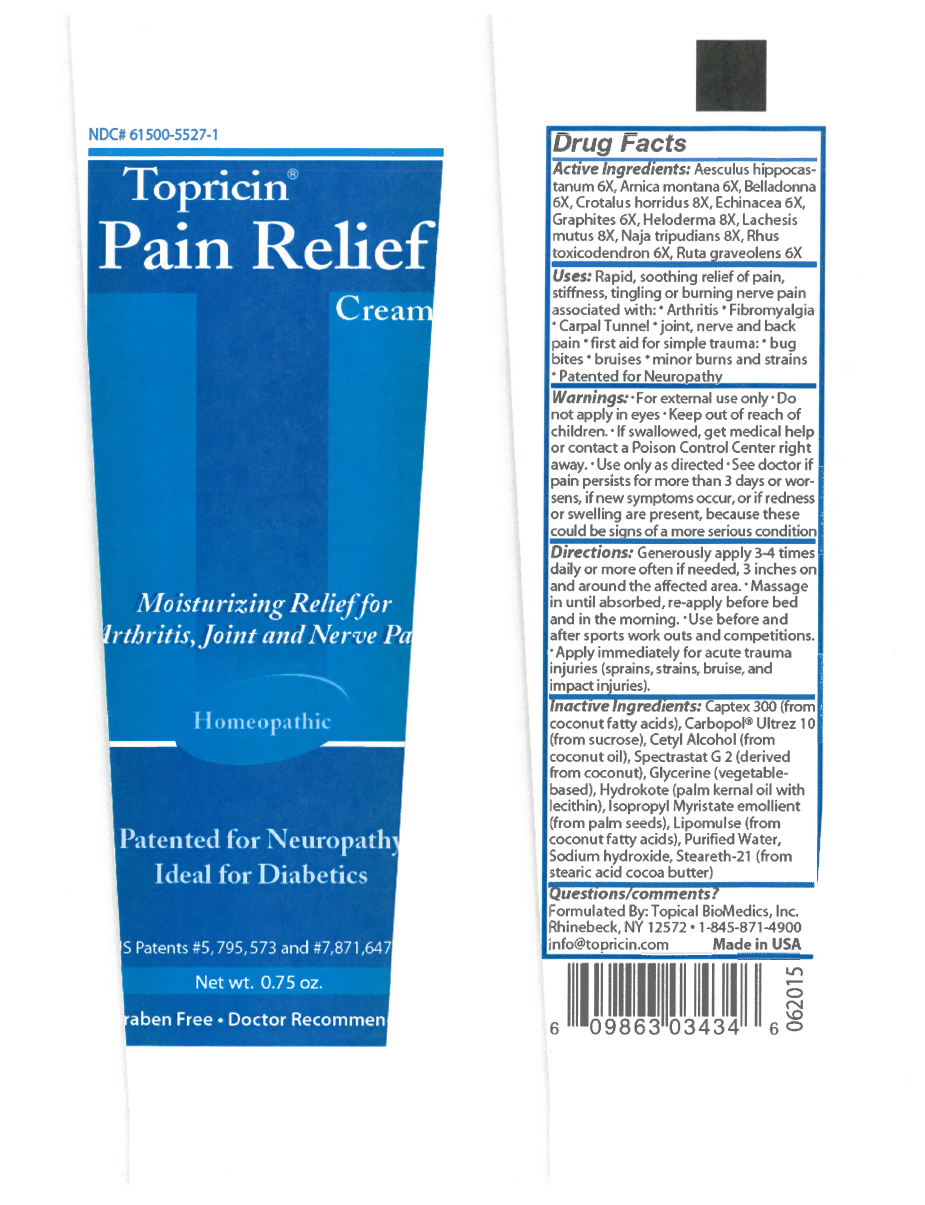 DRUG LABEL: Topricin
NDC: 61500-5527 | Form: CREAM
Manufacturer: Topical BioMedics, Inc.
Category: homeopathic | Type: HUMAN OTC DRUG LABEL
Date: 20251001

ACTIVE INGREDIENTS: AESCULUS HIPPOCASTANUM FLOWER 6 [hp_X]/170 g; ARNICA MONTANA 6 [hp_X]/170 g; CROTALUS HORRIDUS HORRIDUS VENOM 8 [hp_X]/170 g; ECHINACEA ANGUSTIFOLIA 6 [hp_X]/170 g; GRAPHITE 6 [hp_X]/170 g; HELODERMA HORRIDUM VENOM 8 [hp_X]/170 g; LACHESIS MUTA VENOM 8 [hp_X]/170 g; NAJA NAJA VENOM 8 [hp_X]/170 g; RUTA GRAVEOLENS FLOWERING TOP 6 [hp_X]/170 g; ATROPA BELLADONNA 6 [hp_X]/170 g; TOXICODENDRON PUBESCENS LEAF 6 [hp_X]/170 g
INACTIVE INGREDIENTS: CARBOMER INTERPOLYMER TYPE A (ALLYL SUCROSE CROSSLINKED); SODIUM HYDROXIDE; CAPRYLHYDROXAMIC ACID; LECITHIN, SOYBEAN; MEDIUM-CHAIN TRIGLYCERIDES; GLYCERIN; CETYL ALCOHOL; PEG-100 STEARATE; WATER; STEARETH-21; GLYCERYL MONOSTEARATE; HYDROGENATED PALM KERNEL OIL; GLYCERYL CAPRYLATE; ISOPROPYL MYRISTATE

Topricin Pain Relief Cream [0.75oz, 2oz, 4oz, 8oz, 16 oz, 32 oz]

Active Ingredients

Aesculus hippocastanum 6X

Arnica montana 6X

Belladona 6X

Crotalus horridus 8X

Echinacea 6X

Graphites 6X

Heloderma 8X

Lachesis mutus 8X

Naja tripudians 8X

Rhus toxicodendron 6X

Ruta graveolens 6X

Uses

Rapid, soothing relief of pain, stiffness, tingling, or burning nerve pain associated with:

Arthritis and other joint pain and discomfort

Fibromyalgia

Carpal Tunnel Syndrome and other types of nerve pain

Pains & muscle cramps of the back, neck, shoulder, legs, hands & feet

Sports injuries (muscle pulls & soreness, impact, sprains, dislocations)

Repetitive motion injuries, such as bursitis, tendonitis and sciatica

First Aid for simple trauma (bruises, minor burns, cuts, scrapes & strains

Purpose

Relieves pain in the lower back, hip and spine

Treats pain of impact, falling injuries and contusion to muscles and joints

Treats muscle spasms night leg cramps

Relief of impact injuries & deep muscle bruising

Relieves sharp stitching pain in joints & muscles

Relieves skin conditions

Relief of burning pain in the hands and feet

Relief of sciatic pain and carpal tunnel

Relieves nerve injury pain

Pain relief of muscle cramping, joint and post-surgical pain

Relief of injuries to the knee, shin and elbow

Warnings

For external use only. Do not apply in eyes. Ask doctor or pharmacist before using if you are taking a presciption medication. Ask doctor or pharmacist before using if you are pregnant or nursing. Keep all medicines out of reach of children. Use only as directed, see doctor if pain persists for more than 3 days or worsens, if new symptoms occur, or if redness or swelling are present because these could be signs of a more serious condition. Before considering any self help regimen always consult your doctor, especially if you are taking prescription medication.

Directions

Generously apply 3-4 times daily or more often if needed, 3 inches on and around affected area. Massage in until absorbed, re-apply before bedtime and in the morning.

Use before and after sports work outs and other phys9ical acrivities.

Apply immediately for acute trauma injuries (sprain, strain, bruise, and impact injuries).

Inactive Ingredients

Inactive Ingredients: Water/Aqua/Eau, Caprylic/Capric Triglyceride, Isopropyl Myristate, Glycerin, Glyceryl Monostearate SE, Steareth-20, Hydrogenated Vegetable Oil, Caprylhydroxamic Acid, Glyceryl Caprylate, Cetyl Alcohol, Carbomer, Sodium Hydroxide
*Inactive ingredients derived from natural sources

Other Information

This homeopathic medicine is manufactured in the United States at the highest quality standards. Homeopathic medicines are safe, gentle and help your body heal. Safe for children (2-years and above), adults and the elderly. No odor or fragrance, no petroleum, no mineral oil, no lanolin, no capsaicin, no menthol, non-greasy, non-staining and paraben free. Store at room temperature. Tamper Eviden. Do not use if bottle has been opened.For severe injury, always seek medical attention.

Principal Display Panel

NDC# 61500-5527-1

Topricin®

Pain Relief Cream

Moisturizing Relief for Arthritis, Joint and Nerve Pain

Homepathic

Patented for Neuropathy

Ideal for Diabetics

US Patents # 5,795,573 and #7,871,647

Net wt. 0.75 oz.

Paraben Free · Doctor Recommended